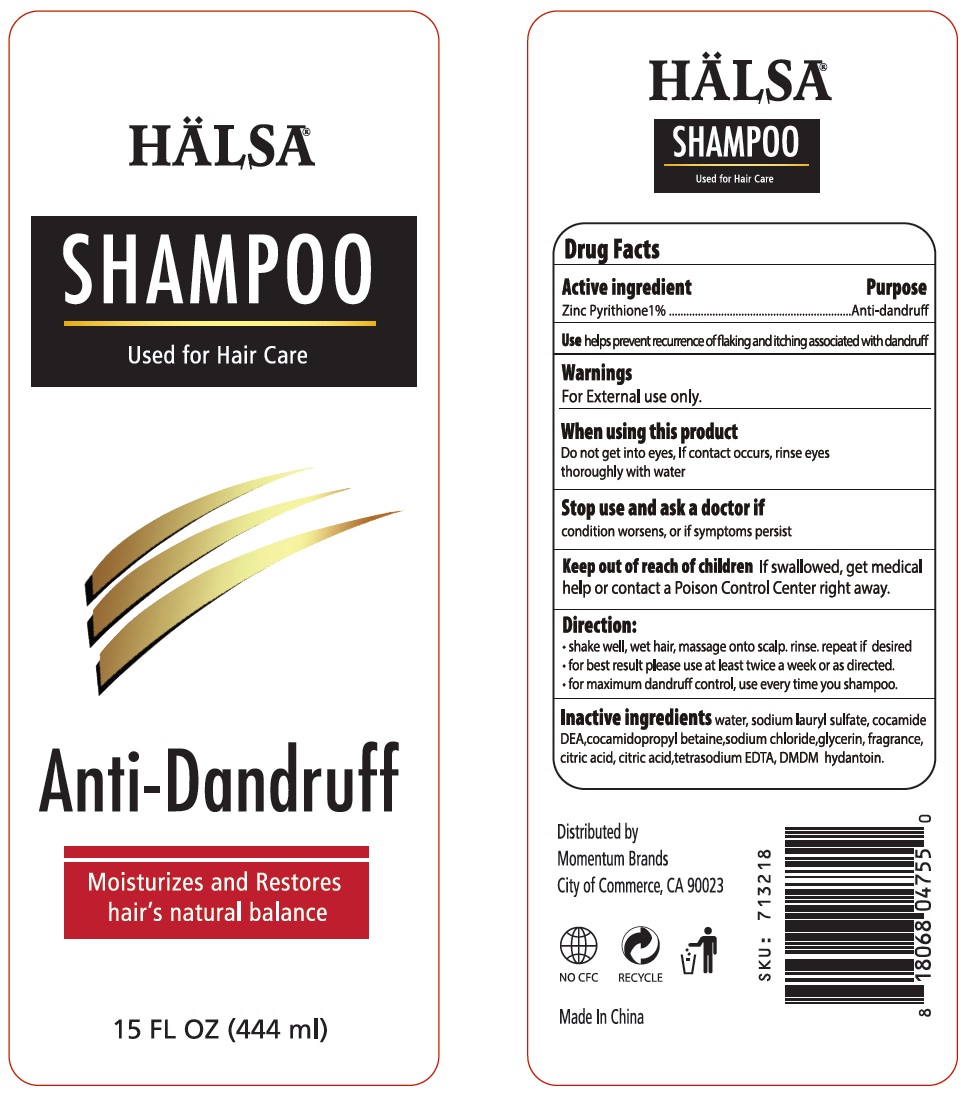 DRUG LABEL: Halsa anti Dandruff
NDC: 40104-380 | Form: SHAMPOO
Manufacturer: NINGBO PULISI DAILY CHEMICAL PRODUCTS CO., LTD.
Category: otc | Type: HUMAN OTC DRUG LABEL
Date: 20170923

ACTIVE INGREDIENTS: PYRITHIONE ZINC 1 g/100 mL
INACTIVE INGREDIENTS: water; cocamidopropyl betaine; glycol stearate; CARBOMER COPOLYMER TYPE A; ammonium chloride; methylchloroisothiazolinone; methylisothiazolinone; CITRIC ACID MONOHYDRATE; EDETATE DISODIUM; FD&C BLUE NO. 1; FD&C YELLOW NO. 5

Drug Facts

Active Ingredient Purpose

Zinc Pyrithione 1% Anti-dandruff

PURPOSE

helps prevent recumence of flaking and itching associated with dandruff

KEEP OUT OF REACH OF CHILDREN

If swallowed, get medical help or contact a Poison Control Center right away.

Do not get into eyes, if contact occurs, rinse eyes thoroughly with water.

INDICATIONS AND USAGE

Shake well, wet hair, massage onto scalp. Rinse, repeat if desired.

For best results, use at least twice a week or as directed.

For maximum dandruff control, use every time you shampoo.

WARNINGS

For external use only.

Stop use and ask a doctor if Condition worsens or if symptoms persist.

DOSAGE AND ADMINISTRATION

shake well, wet hair, massage onto scalp, rinse, repeat if desired.

INACTIVE INGREDIENT

water, sodium laureth sulfate, cocamide DEA, cocamidopropyl betaine, sodium Chloride, Glycerin, Fragrance, citric acid, tetrasodium EDTA, DMDM hydantoin.